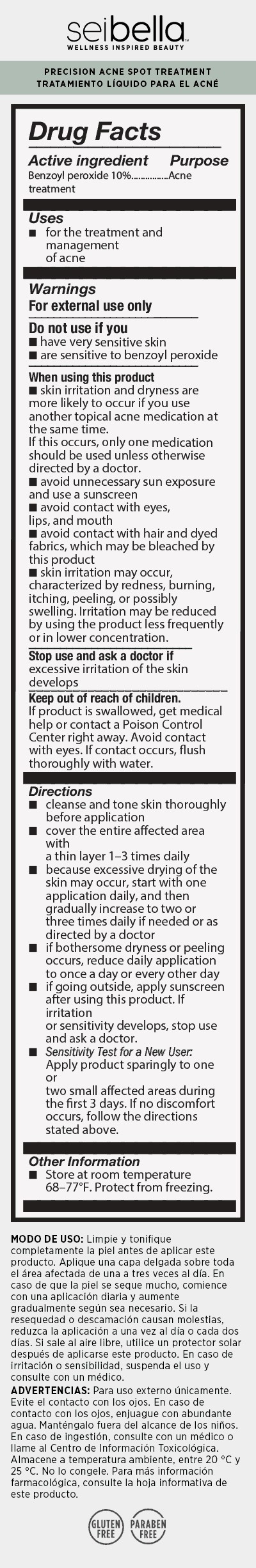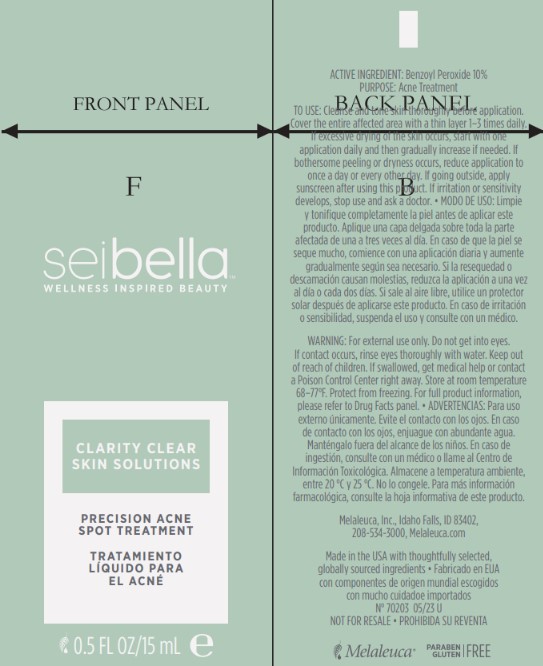 DRUG LABEL: Clarity Clear Skin Solutions
NDC: 54473-402 | Form: CREAM
Manufacturer: Melaleuca, Inc.
Category: otc | Type: HUMAN OTC DRUG LABEL
Date: 20251231

ACTIVE INGREDIENTS: BENZOYL PEROXIDE 1.5 g/15 mL
INACTIVE INGREDIENTS: STEARETH-2; POTASSIUM SORBATE; GLYCERIN; GLYCERYL MONOSTEARATE; ALLANTOIN; PEG-100 STEARATE; CETOSTEARYL ALCOHOL; CHLORELLA VULGARIS; CETYL ALCOHOL; STEARETH-21; PANTHENOL; STEARIC ACID; POLYSORBATE 60; NIACINAMIDE; PHENOXYETHANOL; ETHYL MACADAMIATE; WATER; POLYGLYCERIN-3; LEVOMENOL; XANTHAN GUM

Sei Bella Clarity Clear Precision Acne Spot Treatment

Active Ingredient

Benzoyl peroxide 10%

Purpose

Acne Treatment

INDICATIONS AND USAGE

Uses for the treatment and management of acne

Warnings

For external use only.

Do not use if you

- have very sensitive skin
- are sensitive to benzoyl peroxide

When using this product

- skin irritation and dryness are more likely to occur if you use another topical acne medication at the same time. If this occurs, only one medication should be used unless otherwise directed by a doctor.
- avoid unnecessary sun exposure and use a sunscreen
- avoid contact with eyes, lips, and mouth
- avoid contact with hair and dyed fabrics, which may be bleached by this product
- skin irritation may occur, characterized by redness, burning, itching, peeling, or possibly swelling. Irritation may be reduced by using the product less frequently or in lower concentration.

Stop use and ask a doctor if excessive irritation of the skin develops

Keep out of reach of children. If product is swallowed, get medical help or contact a Poison Control Center right away. Avoid contact with eyes. If contact occurs, flush thoroughly with water.

Directions

- cleanse and tone skin thoroughly before application
- cover the entire affected area with a thin layer 1-3 times daily
- because excessive drying of the skin may occur, start with one application daily, and then gradually increase to two or three times daily if needed or as directed by a doctor
- if bothersome dryness or peeling occurs, reduce daily application to once a day or every other day
- if going outside, apply sunscreen after using this product. If irritation or sensitivity develops, stop use and ask a doctor.
- Sensitivity Test for a New User: Apply product sparingly to one or two small affected areas during the first 3 days. If no discomfort occurs, follow the directions stated above.

Other Information Store at room temperature 68-77°. Protect from freezing.

INACTIVE INGREDIENT

Aqua (Water/Eau), Benzoyl Peroxide Gel, Glycerin, Panthenol, Ethyl Macadamiate, Cetyl Alcohol, Stearic Acid, Niacinamide, Polyglyceryl-3 Methyl Glucose Distearate, Glyceryl Stearate, PEG-100 Stearate, Cetearyl Alcohol, Steareth-21, Phenoxyethanol, Bisabolol, Polysorbate 60, Steareth-2, Xanthan Gum, Allantoin, Potassium Sorbate, Chlorella Vulgaris Extract.